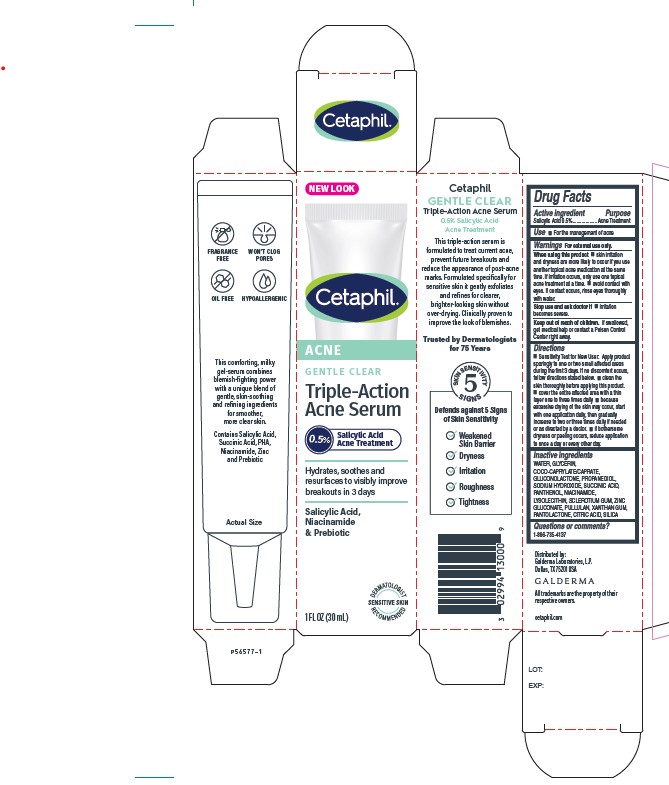 DRUG LABEL: Cetaphil Gentle Clear Triple-Action Acne Serum
NDC: 0299-4135 | Form: SOLUTION
Manufacturer: Galderma Laboratories, L.P.
Category: otc | Type: HUMAN OTC DRUG LABEL
Date: 20231116

ACTIVE INGREDIENTS: Salicylic Acid 5 mg/1 mL
INACTIVE INGREDIENTS: Water; Glycerin; Coco-Caprylate/Caprate; Gluconolactone; Propanediol; Sodium Hydroxide; Succinic Acid; Panthenol; Niacinamide; Lysophosphatidylcholine, Soybean; Betasizofiran; Zinc Gluconate; Pullulan; Xanthan Gum; Pantolactone, (R)-; Citric Acid Monohydrate; Silicon Dioxide

Drug Facts

Active Ingredients

Salicylic Acid 0.5%

Purpose

Acne treatment

Uses

For the management of acne

Warnings

For external use only.

When using this product
■ skin irritation and dryness is more likely to occur if you use another topical acne medication at the same time. If irritation occurs, only use one topical acne treatment at a time. ■ avoid contact with eyes. If contact occurs, rinse eyes thoroughly with water.

Stop use and ask a doctor if
■ irritation becomes severe

Keep out of reach of children.
If swallowed, get medical help or contact a Poison Control Center right away.

Directions

•Sensitivity Test for New User: Apply product sparingly to one or two small affected areas during the first 3 days. If no discomfort occurs, follow directions stated below. • clean the skin thoroughly before applying this product. • cover the entire affected area with a thin layer one to three times daily • because excessive drying of the skin may occur, start with one application daily, then gradually increase to two or three times daily if needed or as directed by a doctor. • if bothersome dryness or peeling occurs, reduce application to once a day or every other day.

Inactive Ingredients

WATER, GLYCERIN, COCO-CAPRYLATE/CAPRATE, GLUCONOLACTONE, PROPANEDIOL, SODIUM HYDROXIDE, SUCCINIC ACID, PANTHENOL, NIACINAMIDE, LYSOLECITHIN, SCLEROTIUM GUM, ZINC GLUCONATE, PULLULAN, XANTHAN GUM, PANTOLACTONE, CITRIC ACID, SILICA

Questions or comments?

1-866-735-4137

QUESTIONS

Distributed by:

Galderma Laboratories, L.P.

Dallas, TX 75201 USA

All trademarks are the property of their respective owners.

cetaphil.com.
P56577-1

Principle Display Panel - 1 FL OZ Carton

NEW LOOK
Cetaphil®

ACNE
GENTLE CLEAR

Triple-Action
Acne Serum
0.5% Salicylic Acid Acne Treatment

Hydrates, soothes and
resurfaces to visibly improve
breakouts in 3 days
Salicylic Acid,
Niacinamide
& Prebiotic
Dermatologist Recommended
Sensitive Skin
1 FL OZ (30 mL)